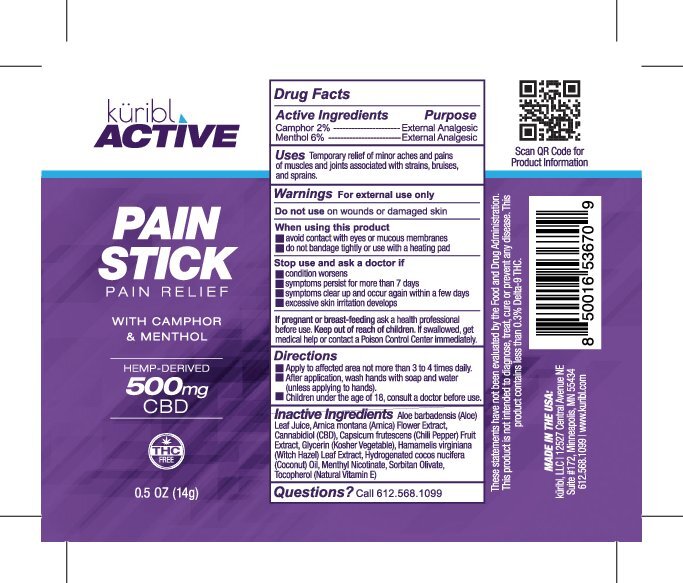 DRUG LABEL: Kuribl Active Pain
NDC: 83111-005 | Form: STICK
Manufacturer: Radiance Beauty & Wellness Inc. dba Saavy Naturals
Category: otc | Type: HUMAN OTC DRUG LABEL
Date: 20230227

ACTIVE INGREDIENTS: CAMPHOR (NATURAL) 2 g/100 g; MENTHOL 6 g/100 g
INACTIVE INGREDIENTS: TABASCO PEPPER; HYDROGENATED COCONUT OIL; GLYCERIN; ALOE VERA LEAF; HAMAMELIS VIRGINIANA LEAF; TOCOPHEROL; SORBITAN OLIVATE; ARNICA MONTANA FLOWER; CANNABIDIOL

Kuribl Active Pain Stick CBD

Active Ingredients Purpose

Camphor 2% External Analgesic

Menthol 6% External Analgesic

PURPOSE

Uses Temporary relief of minor aches and pains of muscles and joints associated with strains, bruises, and sprains.

Keep out of reach of children. If swallowed, get medical help or contact a Poison Control Center immediately

Stop use and ask a doctor if:

- condition worsens
- symptoms persist for more than 7 days
- symptoms clear up and occur again within a few days
- excessive skin irritation develops

Warnings

For external use only

Do not use on wounds or damaged skin

When using this product

- avoid contact with eyes or mucous membranes
- do not bandage tightly or use with a heating pad

If pregnant or breast-feeding ask a health professional before use.

Directions

- Apply to affected area not more than 3 to 4 times daily
- After application wash hands with soap and water (unless applying to hands)
- Children under the age of 18, consult a doctor before use

INACTIVE INGREDIENT

Inactive Ingredients Aloe Barbadensis (Aloe) Leaf Juice, Arnica Montana (Arnica) Flower Extract, Capsicum Frutescens (Chili Pepper) Fruit Extract, Glycerin (Kosher Vegetable), Hamamelis Virginiana (Witch Hazel), Leaf Extract, Hydrogenated cocos nucifera (Coconut) Oil, Menthyl Nicotinate, Sorbitan Olivate, Tocopherol (Natural Vitamin E)

PACKAGE LABEL

kuribl Active

Pain Stick

Pain Relief

With Camphor & Menthol

Hemp-Derived

500mg CBD

0.5 OZ (14 g)